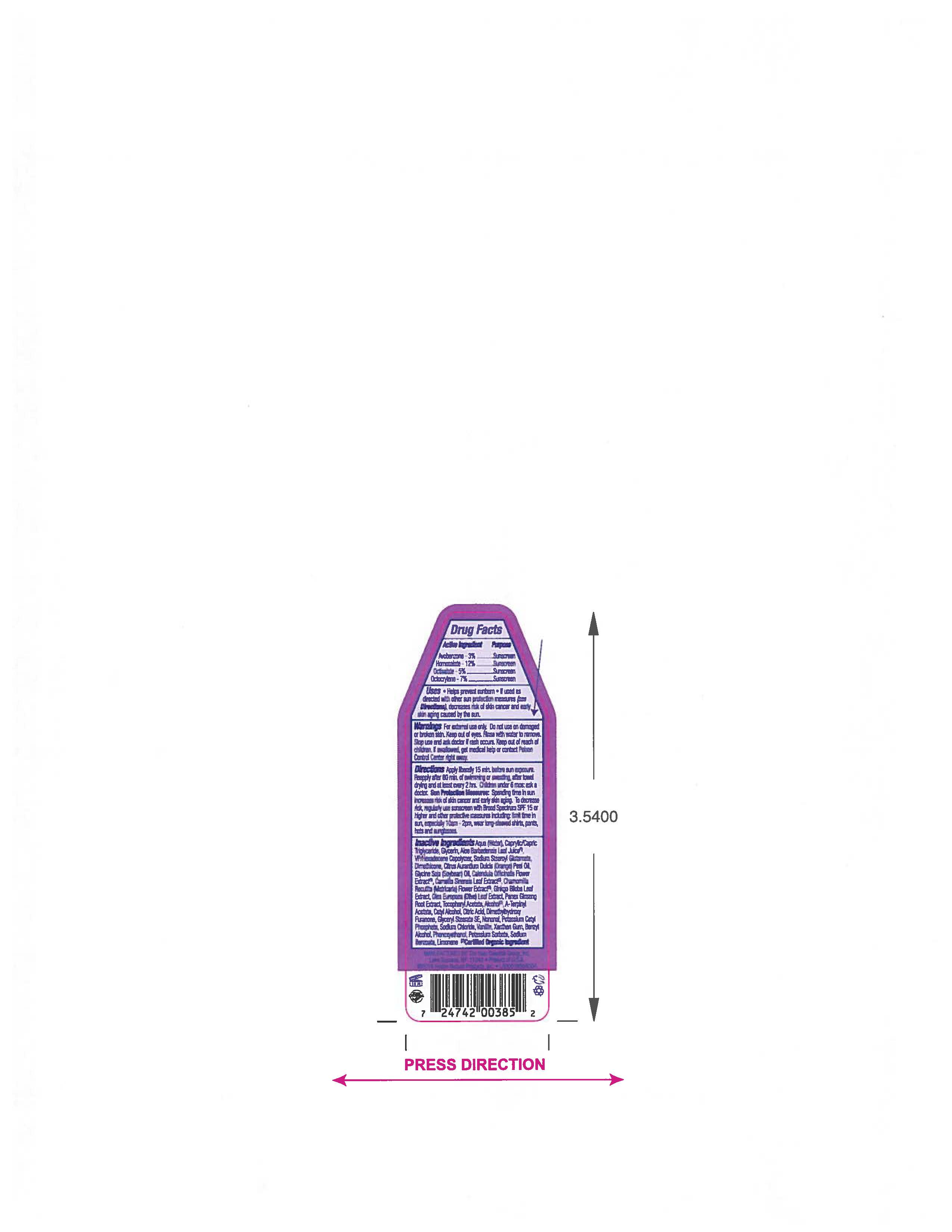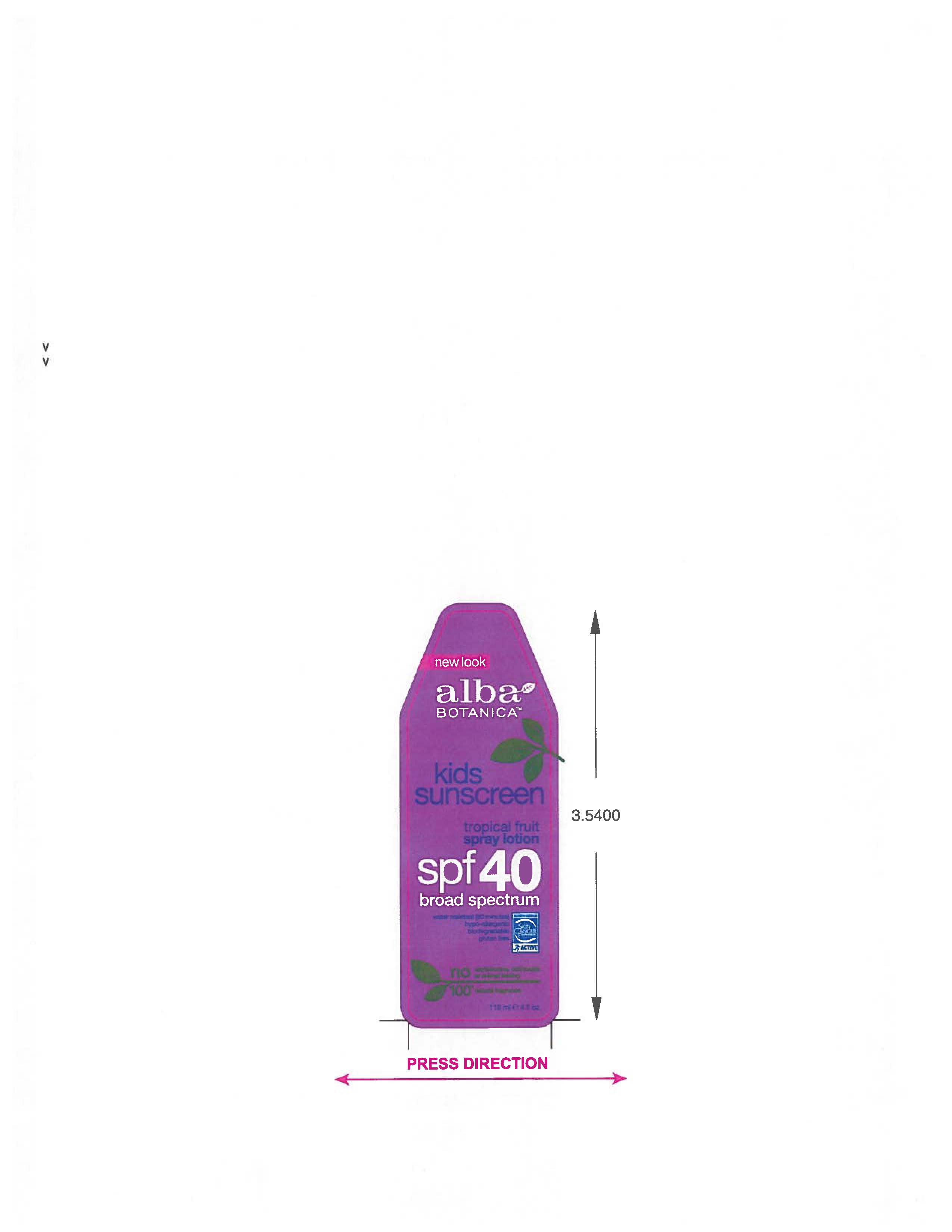 DRUG LABEL: AL0038502 Alba Tropical Fruit Kids Sunscreen SPF40
NDC: 61995-2085 | Form: SPRAY
Manufacturer: The Hain Celestial Group, Inc.
Category: otc | Type: HUMAN OTC DRUG LABEL
Date: 20210412

ACTIVE INGREDIENTS: HOMOSALATE 12 g/100 g; OCTOCRYLENE 7 g/100 g; OCTISALATE 5 g/100 g; AVOBENZONE 3 g/100 g
INACTIVE INGREDIENTS: VINYLPYRROLIDONE/HEXADECENE COPOLYMER; MEDIUM-CHAIN TRIGLYCERIDES; WATER; GLYCERIN; SODIUM STEAROYL GLUTAMATE; DIMETHICONE; ALOE VERA LEAF; CALENDULA OFFICINALIS FLOWER; GREEN TEA LEAF; CHAMOMILE; OLEA EUROPAEA LEAF; GINKGO; ASIAN GINSENG; CETYL ALCOHOL; GLYCERYL MONOSTEARATE; CITRIC ACID MONOHYDRATE; POTASSIUM CETYL PHOSPHATE; SODIUM CHLORIDE; .ALPHA.-TOCOPHEROL ACETATE; XANTHAN GUM; ALCOHOL; BENZYL ALCOHOL; PHENOXYETHANOL; POTASSIUM SORBATE; SODIUM BENZOATE; ORANGE OIL; SOYBEAN OIL; TERPINYL ACETATE; DIMETHYLHYDROXY FURANONE; NONANAL; VANILLIN; LIMONENE, (+)-

Alba Botanica Kids Sunscreen Spray Lotion SP F40

ACTIVE INGREDIENT

Avobenzone -3%

Homosalate -12.0%

Octocrylene - 7.0%

Octyl Salicylate - 5.0%

PURPOSE

Sunscreen

INDICATIONS AND USAGE

- Helps prevent sunburn. If used as directed with other sun protection measures, decreases risk of skin cancer and early skin aging caused by sun.

WARNINGS

For external use only. Do not use on damaged or broken skin. Keep out of eyes.Rinse with water to remove. Stop use and ask a doctor if skin rash occurs.

Keep out of reach of children. If swallowed, get medical help or contact a Poison Control Center right away

DOSAGE AND ADMINISTRATION

Apply liberally 15 minutes before sun exposure. Reapply after 80 min of swimming or sweating,after towel drying and at lease every two hrs. Children under 6 mos: ask a doctor.

Skin protection measures:

Spending time in the sun increases your risk of skin cancer and early skin aging. To decrease a risk,regularly use a Sunscreen with Broad Spectrum SPF 15 or higher and other protective measures including: limit time in sun, especially 10am- 2pm, wear long- sleeved shirts,pants, hats and sunglasses.

INACTIVE INGREDIENT

Aqua (Water), Caprylic/Capric Triglyceride, Glycerin, Aloe Barbadensis Leaf Juice (1), VP/Hexadecene Copolymer, Sodium Stearoyl Glutamate, Dimethicone, Citrus Aurantium Dulcis (Orange) Peel Oil, Glycine Soja (Soybean) Oil, Calendula Officinalis Flower Extract (1), Camellia Sinensis Leaf Extract (1), Chamomilla Recuitita (Matricaria) Flower Extract (1), Gingko Biloba Root Extract, Olea Europaea (Olive) Leaf Extract, Panax Ginseng Root Extract (1), Tocopheryl Acetate, Alcohol (1), A-Terpinyl Acetate, Cetyl Alcohol, Citric Acid, Dimethylhydroxy Furanone, Glyceryl Stearate SE, Nonanal, Potassium Cetyl Phosphate, Sodium Chloride, Vanillin, Xanthan Gum, Benzyl Alcohol, Phenoxyethanol, Potassium Sorbate, Sodium Benzoate, Limonene.

(1) Certified Organic Ingredient

QUESTIONS

888-659-7730, www.AlbaBotanica.com